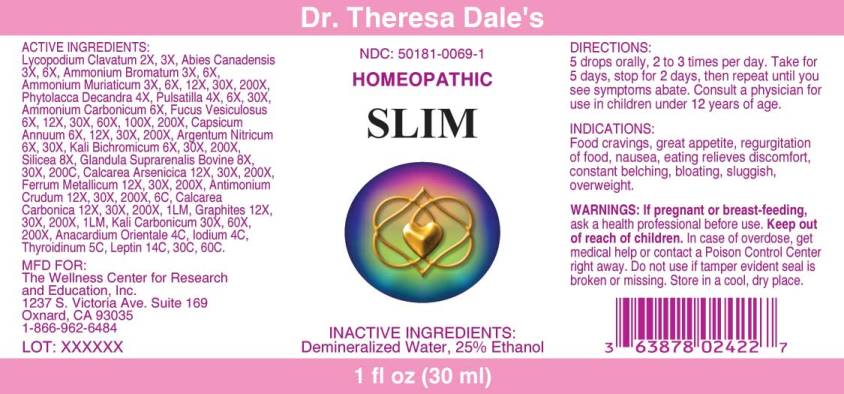 DRUG LABEL: SLIM
NDC: 50181-0069 | Form: LIQUID
Manufacturer: The Wellness Center for Research and Education
Category: homeopathic | Type: HUMAN OTC DRUG LABEL
Date: 20250606

ACTIVE INGREDIENTS: LYCOPODIUM CLAVATUM SPORE 2 [hp_X]/1 mL; TSUGA CANADENSIS BARK 3 [hp_X]/1 mL; AMMONIUM BROMIDE 3 [hp_X]/1 mL; AMMONIUM CHLORIDE 3 [hp_X]/1 mL; PHYTOLACCA AMERICANA ROOT 4 [hp_X]/1 mL; PULSATILLA PRATENSIS WHOLE 4 [hp_X]/1 mL; AMMONIUM CARBONATE 6 [hp_X]/1 mL; FUCUS VESICULOSUS 6 [hp_X]/1 mL; CAPSICUM 6 [hp_X]/1 mL; SILVER NITRATE 6 [hp_X]/1 mL; POTASSIUM DICHROMATE 6 [hp_X]/1 mL; SILICON DIOXIDE 8 [hp_X]/1 mL; BOS TAURUS ADRENAL GLAND 8 [hp_X]/1 mL; CALCIUM ARSENATE 12 [hp_X]/1 mL; IRON 12 [hp_X]/1 mL; ANTIMONY TRISULFIDE 12 [hp_X]/1 mL; OYSTER SHELL CALCIUM CARBONATE, CRUDE 12 [hp_X]/1 mL; GRAPHITE 12 [hp_X]/1 mL; POTASSIUM CARBONATE 30 [hp_X]/1 mL; SEMECARPUS ANACARDIUM JUICE 4 [hp_C]/1 mL; IODINE 4 [hp_C]/1 mL; THYROID 5 [hp_C]/1 mL; LEPTIN HUMAN 14 [hp_C]/1 mL
INACTIVE INGREDIENTS: WATER; ALCOHOL

DRUG FACTS:

ACTIVE INGREDIENTS:

Lycopodium Clavatum 2X, 3X, Abies Canadensis 3X, 6X, Ammonium Bromatum 3X, 6X, Ammonium Muriaticum 3X, 6X, 12X, 30X, 200X, Phytolacca Decandra 4X, Pulsatilla (Pratensis) 4X, 6X, 30X, Ammonium Carbonicum 6X, Fucus Vesiculosus 6X, 12X, 30X, 60X, 100X, 200X, Capsicum Annuum 6X, 12X, 30X, 200X, Argentum Nitricum 6X, 30X, Kali Bichromicum 6X, 30X, 200X, Silicea 8X, Glandula Suprarenalis Bovine 8X, 30X, 200C, Calcarea Arsenicica 12X, 30X, 200X, Ferrum Metallicum 12X, 30X, 200X, Antimonium Crudum 12X, 30X, 200X, 6C, Calcarea Carbonica 12X, 30X, 200X, 1LM, Graphites 12X, 30X, 200X, 1LM, Kali Carbonicum 30X, 60X, 200X, Anacardium Orientale 4C, Iodium 4C, Thyroidinum (Suis) 5C, Leptin, 14C, 30C, 60C.

INDICATIONS:

Food cravings, great appetite, regurgitation of food, nausea, eating relieves discomfort, constant belching, bloating, sluggish, overweight.

WARNINGS:

If pregnant or breast-feeding, ask a health professional before use.

Keep out of reach of children. In case of overdose, get medical help or contact a Poison Control Center right away.

Do not use if tamper evident seal is broken or missing. Store in a cool, dry place.

Keep out of reach of children. In case of overdose, get medical help or contact a Poison Control Center right away.

DIRECTIONS:

5 drops orally, 2 to 3 times per day. Take for 5 days, stop for 2 days, then repeat until you see symptoms abate. Consult a physician for use in children under 12 years of age.

INDICATIONS:

Food cravings, great appetite, regurgitation of food, nausea, eating relieves discomfort, constant belching, bloating, sluggish, overweight.

INACTIVE INGREDIENTS:

Demineralized Water, 25% Ethanol

QUESTIONS:

MFD FOR:

The Wellness Center for Research

and Education, Inc.

1237 S. Victoria Ave. Suite 169

Oxnard, CA 93035

1-866-962-6484

PACKAGE LABEL DISPLAY:

Dr. Theresa Dale's

NDC: 50181-0069-1

HOMEOPATHIC

SLIM

1 fl oz (30 ml)